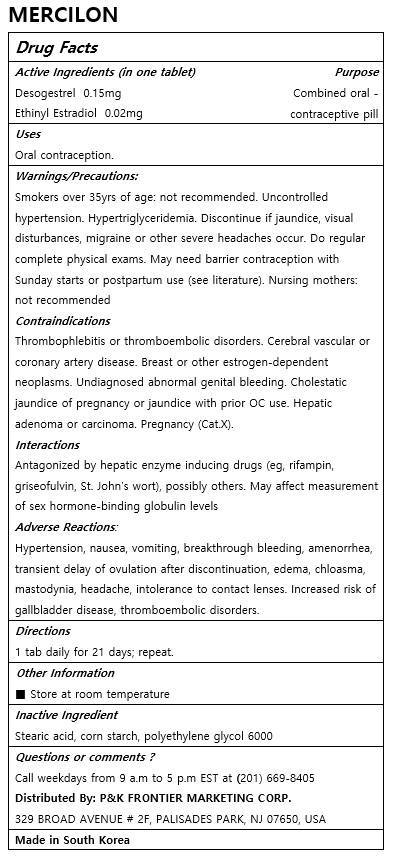 DRUG LABEL: MERCILON
NDC: 72689-0020 | Form: TABLET
Manufacturer: OASIS TRADING
Category: otc | Type: HUMAN OTC DRUG LABEL
Date: 20181211

ACTIVE INGREDIENTS: DESOGESTREL 0.15 mg/1 1; ETHINYL ESTRADIOL 0.02 mg/1 1
INACTIVE INGREDIENTS: STEARIC ACID; STARCH, CORN; POLYETHYLENE GLYCOL 6000

ACTIVE INGREDIENT

Desogestrel, Ethinyl Estradiol

PURPOSE

Oral contraception

Keep out of reach of children

INDICATIONS AND USAGE

1 tab daily for 21 days; repeat.

Warnings/Precautions:

Smokers over 35yrs of age: not recommended. Uncontrolled hypertension. Hypertriglyceridemia. Discontinue if jaundice, visual disturbances, migraine or other severe headaches occur. Do regular complete physical exams. May need barrier contraception with Sunday starts or postpartum use (see literature). Nursing mothers: not recommended

Contraindications

Thrombophlebitis or thromboembolic disorders. Cerebral vascular or coronary artery disease. Breast or other estrogen-dependent neoplasms. Undiagnosed abnormal genital bleeding. Cholestatic jaundice of pregnancy or jaundice with prior OC use. Hepatic adenoma or carcinoma. Pregnancy (Cat.X).

Interactions

Antagonized by hepatic enzyme inducing drugs (eg, rifampin, griseofulvin, St. John's wort), possibly others. May affect measurement of sex hormone-binding globulin levels

Adverse Reactions:

Hypertension, nausea, vomiting, breakthrough bleeding, amenorrhea, transient delay of ovulation after discontinuation, edema, chloasma, mastodynia, headache, intolerance to contact lenses. Increased risk of gallbladder disease, thromboembolic disorders.

INACTIVE INGREDIENT

Stearic acid, corn starch, polyethylene glycol 6000

DOSAGE AND ADMINISTRATION

For oral use only